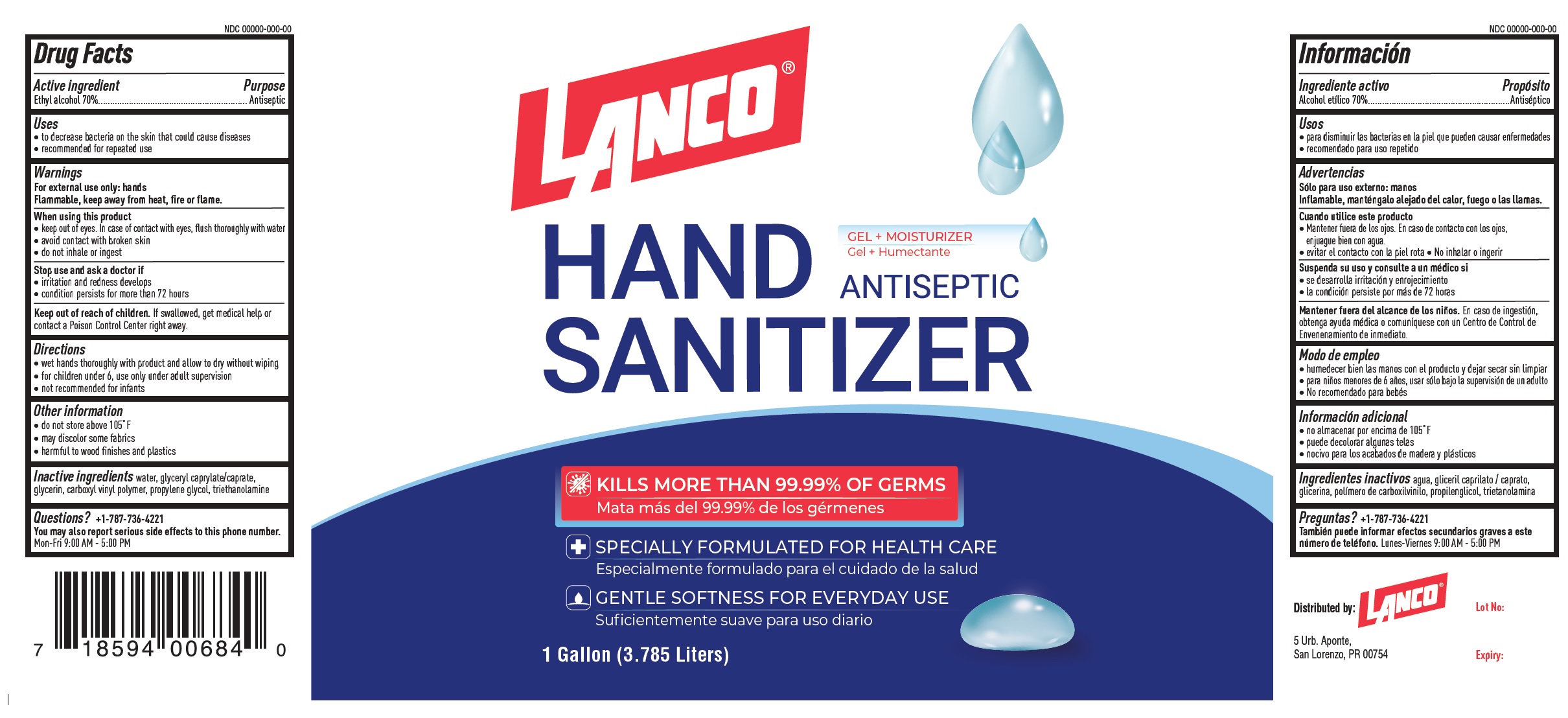 DRUG LABEL: Lanco Antiseptic Hand Sanitizer
NDC: 80522-001 | Form: LIQUID
Manufacturer: Lanco Manufacturing, Corp.
Category: otc | Type: HUMAN OTC DRUG LABEL
Date: 20201209

ACTIVE INGREDIENTS: ALCOHOL 0.7 mL/1 mL
INACTIVE INGREDIENTS: WATER; GLYCERYL MONOCAPRYLOCAPRATE; GLYCERIN; PROPYLENE GLYCOL; TROLAMINE

Lanco Antiseptic Hand Sanitizer

Active ingredient

Ethyl alcohol 70%

Purpose

Antiseptic

Uses

- to decrease bacteria on the skin that could cause diseases
- Recommended for repeated use

Warnings

For external use only: hands
Flammable, keep away from heat, fire or flame.

When using this product

- keep out of eyes. In case of contact with eyes, flush thoroughly with water
- avoid contact with broken skin
- do not inhale or ingest

Stop use and ask a doctor if

- Irritation and redness develop
- Condition persists for more than 72 hours

Keep out of reach of children.

If swallowed, get medical help or contact a Poison Control Center right away.

Directions

- Wet hands thoroughly with product and allow to dry without wiping
- for children under 6, use only under adult supervision
- not recommended for infants

Other information

- do not Store above 105° F
- may discolor some fabrics
- harmful to wood finishes and plastics

Inactive ingredients

water, glyceryl caprylate/caprate, glycerin, carboxyl vinyl polymer, propylene glycol, triethanolamine

Questions?

+1-787-736-4221

You may also report serious side effects to this phone number

Mon-Fri 9:00 AM - 5:00 PM